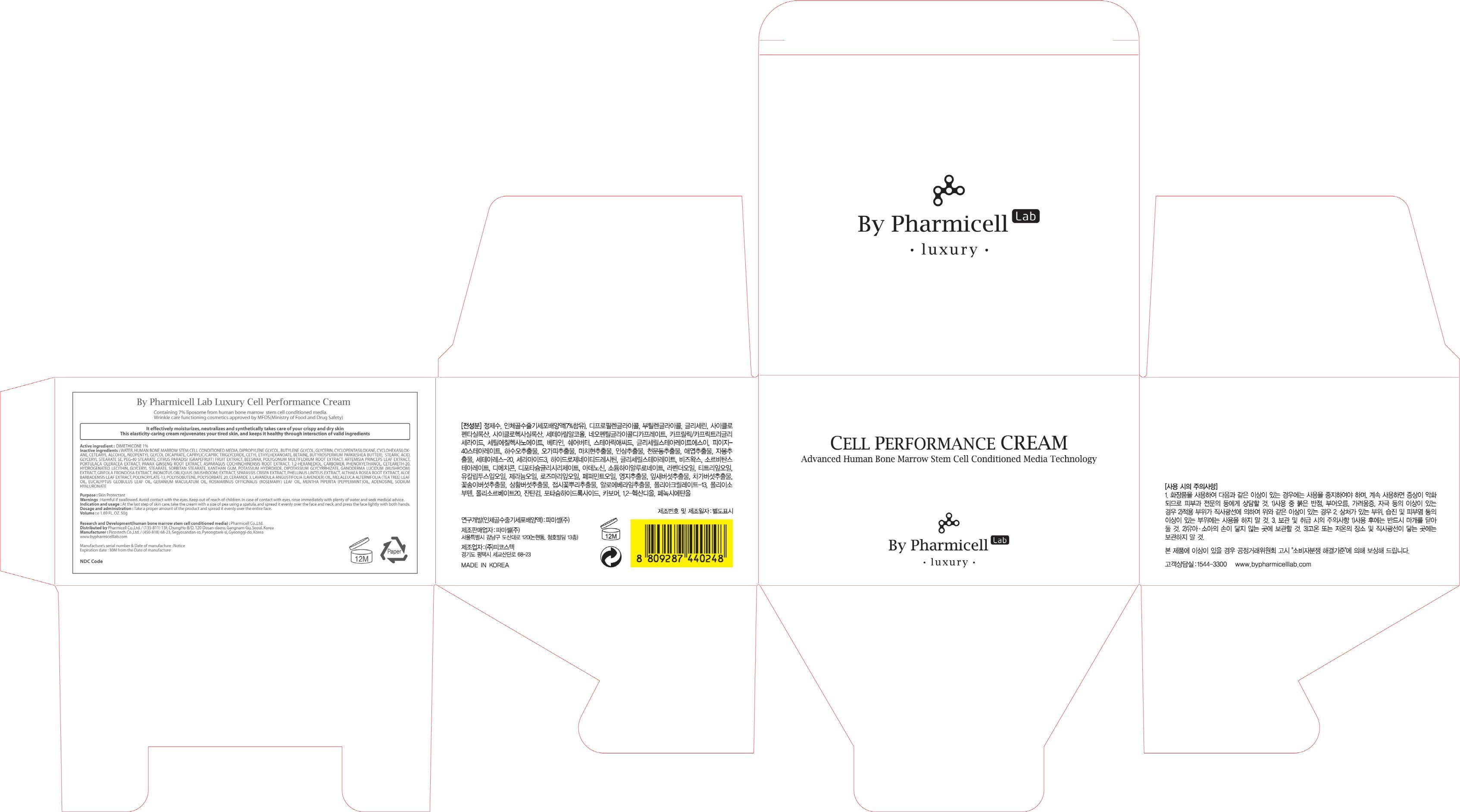 DRUG LABEL: Luxury Cell Performance
NDC: 60949-160 | Form: CREAM
Manufacturer: Pharmicell Co., Ltd.
Category: otc | Type: HUMAN OTC DRUG LABEL
Date: 20140922

ACTIVE INGREDIENTS: DIMETHICONE 0.5 g/50 g
INACTIVE INGREDIENTS: WATER; DIPROPYLENE GLYCOL

ACTIVE INGREDIENT

Active ingredient : DIMETHICONE 1%

INACTIVE INGREDIENT

Inactive ingredients : WATER, HUMAN BONE MARROW STEM CELL CONDITIONED MEDIA, DIPROPYLENE GLYCOL, BUTYLENE GLYCOL, GLYCERIN, CYCLOPENTASILOXANE, CYCLOHEXASILOXANE, CETEARYL ALCOHOL, NEOPENTYL GLYCOL DICAPRATE, CAPRYLIC/CAPRIC TRIGLYCERIDE, CETYL ETHYLHEXANOATE, BETAINE, BUTYROSPERMUM PARKII(SHEA BUTTER),
STEARIC ACID, GLYCERYL STEARATE SE, PEG-40 STEARATE, CITRUS PARADISI (GRAPEFRUIT) FRUIT EXTRACT, BEESWAX, POLYGONUM MULTIFLORUM ROOT EXTRACT, ARTEMISIA PRINCEPS LEAF EXTRACT, PORTULACA OLERACEA EXTRACT, PANAX GINSENG ROOT EXTRACT, ASPARAGUS COCHINCHINENSIS ROOT EXTRACT, 1,2-HEXANEDIOL, CARBOMER, PHENOXYETHANOL, CETEARETH-20, HYDROGENATED LECITHIN, GLYCERYL STEARATE, SORBITAN STEARATE, XANTHAN GUM, POTASSIUM HYDROXIDE, DIPOTASSIUM GLYCYRRHIZATE, GANODERMA LUCIDUM (MUSHROOM) EXTRACT, GRIFOLA FRONDOSA EXTRACT, INONOTUS OBLIQUUS (MUSHROOM) EXTRACT, SPARASSIS CRISPA EXTRACT, PHELLINUS LINTEUS EXTRACT, ALTHAEA ROSEA ROOT EXTRACT, ALOE BARBADENSIS LEAF EXTRACT, POLYACRYLATE-13, POLYISOBUTENE, POLYSORBATE 20, CERAMIDE 3, LAVANDULA ANGUSTIFOLIA (LAVENDER) OIL, MELALEUCA ALTERNIFOLIA (TEA TREE) LEAF OIL, EUCALYPTUS GLOBULUS LEAF OIL, GERANIUM MACULATUM OIL, ROSMARINUS OFFICINALIS (ROSEMARY) LEAF OIL, MENTHA PIPERITA (PEPPERMINT)OIL, ADENOSINE, SODIUM HYALURONATE

PURPOSE

Purpose : Skin Protectant

WARNINGS

Warnings : Harmful if swallowed. Avoid contact with the eyes. Keep out of reach of children. In case of contact with eyes, rinse immediately with plenty of water and seek medical advice.

KEEP OUT OF REACH OF CHILDREN

INDICATIONS & USAGE

Indication and usage : At the last step of skin care, take the cream with a size of pea using a spatula, and spread it evenly over the face and neck, and press the face lightly with both hands.

DOSAGE & ADMINISTRATION

Dosage and administration : Take a proper amount of the product and spread it evenly over the entire face.